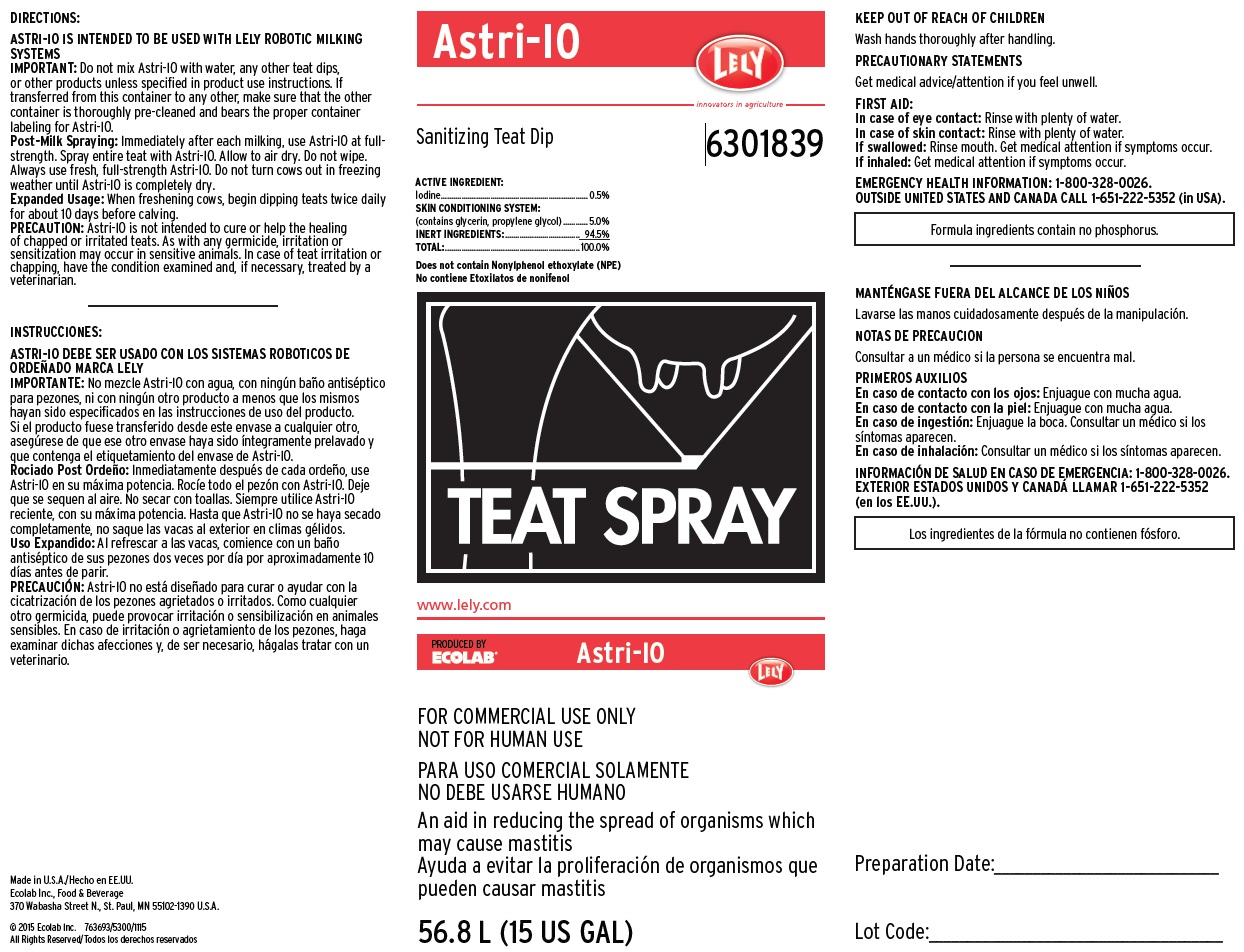 DRUG LABEL: Astri-IO
NDC: 47593-475 | Form: SOLUTION
Manufacturer: Ecolab Inc. 
Category: animal | Type: OTC ANIMAL DRUG LABEL
Date: 20230601

ACTIVE INGREDIENTS: IODINE 5 mg/1 mL
INACTIVE INGREDIENTS: WATER; GLYCERIN; PROPYLENE GLYCOL

KEEP OUT OF REACH OF CHILDREN

Wash hands thoroughly after handling.

PRECAUTIONARY STATEMENTS

Get medical advice/attention if you feel unwell.

FOR COMMERCIAL USE ONLY

NOT FOR HUMAN USE

DIRECTIONS:

ASTRI-IO IS INTENDED TO BE USED WITH LELY ROBOTIC MILKING SYSTEMS

IMPORTANT: Do not mix Astri-IO with water, any other teat dips, or other products unless specified in product use instructions. If transferred from this container to any other, make sure that the other container is thoroughly pre-cleaned and bears the proper container labeling for Astri-IO.

Post-Milk Spraying: Immediately after each milking, use Astri-IO at fullstrength. Spray entire teat with Astri-IO. Allow to air dry. Do not wipe.

Always use fresh, full-strength Astri-IO. Do not turn cows out in freezing weather until Astri-IO is completely dry.

Expanded Usage: When freshening cows, begin dipping teats twice daily for about 10 days before calving.

PRECAUTION: Astri-IO is not intended to cure or help the healing of chapped or irritated teats. As with any germicide, irritation or

sensitization may occur in sensitive animals. In case of teat irritation or chapping, have the condition examined and, if necessary, treated by a

veterinarian.

OTHER SAFETY INFORMATION

FIRST AID:

In case of eye contact: Rinse with plenty of water.

In case of skin contact: Rinse with plenty of water.

If swallowed: Rinse mouth. Get medical attention if symptoms occur.

If inhaled: Get medical attention if symptoms occur.

EMERGENCY HEALTH INFORMATION: 1-800-328-0026.

OUTSIDE UNITED STATES AND CANADA CALL 1-651-222-5352 (in USA).

Representative label & principal display panel

Astri-IO

Lely

Sanitizing Teat Dip 6301839

ACTIVE INGREDIENT:

Iodine....................................................... 0.5%

SKIN CONDITIONING SYSTEM:

(contains glycerin, propylene glycol)............. 5.0%

INERT INGREDIENTS:............................ 94.5%

TOTAL:................................................. 100.0%

Does not contain Nonylphenol ethoxylate (NPE)

Formula ingredients contain no phosphorus

www.lely.com

Produced by Ecolab Astri-IO Lely

FOR COMMERCIAL USE ONLY

NOT FOR HUMAN USE

An aid in reducing the spread of organisms which may cause mastitis

56.8 L (15 US GAL)

Made in U.S.A.

Ecolab Inc., Food & Beverage

370 Wabasha Street N., St. Paul, MN 55102-1390 U.S.A.

© 2015 Ecolab Inc. 763693/5300/1115

All Rights Reserved